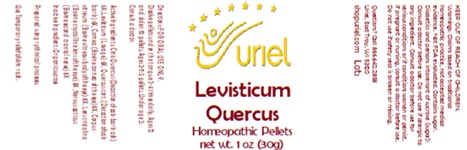 DRUG LABEL: Levisticum Quercus
NDC: 48951-6032 | Form: PELLET
Manufacturer: Uriel Pharmacy Inc.
Category: homeopathic | Type: HUMAN OTC DRUG LABEL
Date: 20250127

ACTIVE INGREDIENTS: QUERCUS ROBUR WHOLE 6 [hp_X]/1 1; BOS TAURUS EYE 6 [hp_X]/1 1; LEVISTICUM OFFICINALE ROOT 6 [hp_X]/1 1
INACTIVE INGREDIENTS: SUCROSE

Levisticum Quercus

INDICATIONS AND USAGE

Directions: FOR ORAL USE ONLY.

DOSAGE AND ADMINISTRATION

Dissolve pellets under the tongue 3-4 times daily. Ages 12 and older: 10 pellets. Ages 2-11: 5 pellets. Under age 2: Consult a doctor.

ACTIVE INGREDIENT

Active Ingredients: Cinis Quercus (Decoction of oak bark ash) 6X, Cornea (Bovine cornea of the eye) 6X, Corpus vitreum (Bovine vitreous body of the eye) 6X, Lens cristalina (Bovine crystalline lens of the eye) 6X, Levisticum (Lovage) 6X, Nervus opticus (Bovine second cranial nerve) 6X, Quercus cort. (Decoction of oak bark) 6X

Inactive Ingredient: Organic sucrose

Prepared using rhythmical processes.

PURPOSE

Use: Temporary relief of skin rash.

KEEP OUT OF REACH OF CHILDREN.

WARNINGS

Warnings: Claims based on traditional homeopathic practice, not accepted medical evidence. Not FDA evaluated. Contains sugar. Diabetics and persons intolerant of sucrose (sugar): Consult a doctor before use. Do not use if allergic to any ingredient. Consult a doctor before use for serious conditions or if conditions worsen or persist. If pregnant or nursing, consult a doctor before use. Do not use if safety seal is broken or missing.

Questions? Call 866.642.2858
Uriel, East Troy, WI 53120
shopuriel.com Lot: